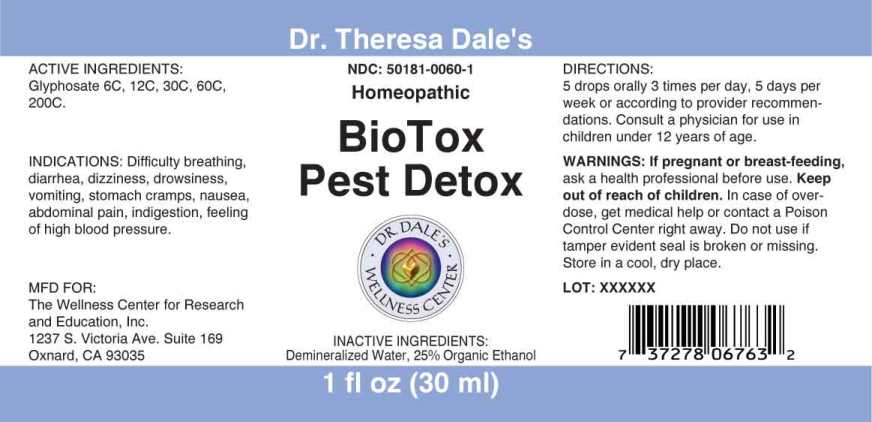 DRUG LABEL: BioTox Pest Detox
NDC: 50181-0060 | Form: LIQUID
Manufacturer: The Wellness Center For Research and Education
Category: homeopathic | Type: HUMAN OTC DRUG LABEL
Date: 20250530

ACTIVE INGREDIENTS: GLYPHOSATE 6 [hp_C]/1 mL
INACTIVE INGREDIENTS: WATER; ALCOHOL

Drug Facts:

ACTIVE INGREDIENTS:

Glyphosate 6C, 12C, 30C, 60C, 200C.

INDICATIONS:

Difficulty breathing, diarrhea, dizziness, drowsiness, vomiting, stomach cramps, nausea, abdominal pain, indigestion, feeling of high blood pressure.

WARNINGS:

If you are pregnant or breastfeeding, ask a health professional before use.

Keep out of reach of children. In case of overdose, get medical help or contact a Poison Control Center right away.

Do not use if tamper evident seal is broken or missing.

Store in a cool, dry place.

Keep out of reach of children. In case of overdose, get medical help or contact a Poison Control Center right away.

DIRECTIONS:

5 drops orally 3 times per day, 5 days per week, or according to provider recommendations. Consult a physician for use in children under 12 years of age.

INDICATIONS:

Difficulty breathing, diarrhea, dizziness, drowsiness, vomiting, stomach cramps, nausea, abdominal pain, indigestion, feeling of high blood pressure.

INACTIVE INGREDIENTS:

Demineralized Water, 25% Organic Ethanol

QUESTIONS:

MFD FOR:

The Wellness Center for

Research and Education, Inc.

1237 S. Victoria Ave. Suite 169

Oxnard, CA 93035

PACKAGE LABEL DISPLAY:

Dr. Theresa Dale's

NDC 50181-0060-1

Homeopathic

BioTox

Pest Detox

1 fl oz (30 ml)